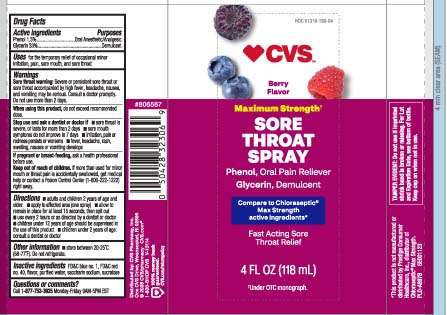 DRUG LABEL: Sore Throat
NDC: 51316-199 | Form: SPRAY
Manufacturer: CVS PHARMACY, INC
Category: otc | Type: HUMAN OTC DRUG LABEL
Date: 20260302

ACTIVE INGREDIENTS: PHENOL 1.5 mg/100 mL; GLYCERIN 33 mg/100 mL
INACTIVE INGREDIENTS: FD&C BLUE NO. 1; FD&C RED NO. 40; SUCRALOSE; WATER; SACCHARIN SODIUM

Drug Facts

Active ingredients

Phenol 1.5%

Glycerin 33%

Purpose

Oral Anesthetic/Analgesic

Demulcent

Uses

for the temporarily relief of occasional minor irritation, pain, sore mouth, and sore throat

Warnings

Sore throat warning: Severe or persistent sore throat or sore throat accompanied by high fever, headache, nausea, and vomiting may be serious. Consult a doctor promptly. Do not use more than 2 days.

When using this product,

do not exceed recommended dose.

Stop use and ask a dentist or doctor if

- sore throat is severe, or lasts for more than 2 days
- sore mouth symptoms do not improve in 7 days
- irritation, pain or redness persists or worsens
- fever, headache, rash, swelling, nausea or vomiting develops

If pregnant or breast-feeding,

ask a health professional before use.

Keep out of reach of children.

if more than used for minor mouth or throat pain is accidentally swallowed, get medical help or contact a Poison Control Center (1-800-222-1222) right away.

Directions

- adults and children 2 years of age and older:
  - apply to affected area (one spray)
  - allow to remain in place for at least 15 seconds, then spit out
  - use every 2 hours as directed by a dentist or doctor
- children under 12 years of age should be supervised in the use of this product
- children under 2 years of age: consult a dentist or doctor

Other information

- store between 20-25ºC (68-77ºF). Do not refrigerate.

Inactive ingredients

FD&C blue # 1, FD&C red #40, flavor, purified water, saccharin sodium, sucralose

Questions or comments?

Call 1-877-753-3935 Monday-Friday 9AM-5PM EST

Principal Display Panel

Compare to Chloraseptic® Max Strength active ingredients*

Maximum Strength†

SORE THROAT SPRAY

Phenol, Oral Pain Reliever

Glycerin, Demulcent

Fast Acting Sore Throat Relief

Berry Flavored

FL OZ (mL)

*This product is not manufactured or distributed by Prestige Consumer Healthcare, Inc, distributor of Chloraseptic® Max Strength.

TAMPER EVIDENT: Do not use if imprinted shrink band is broken or missing. For Lot and Expiration Date, see bottom of bottle. Keep cap on when not in use.

Distributed by: CVS Pharmacy, Inc.

One CVS Drive, Woonsocket, RI 02895

© 2026 CVS/pharmacy CVS.com®

Package Label

CVS Sore Throat Spray Berry Flavor